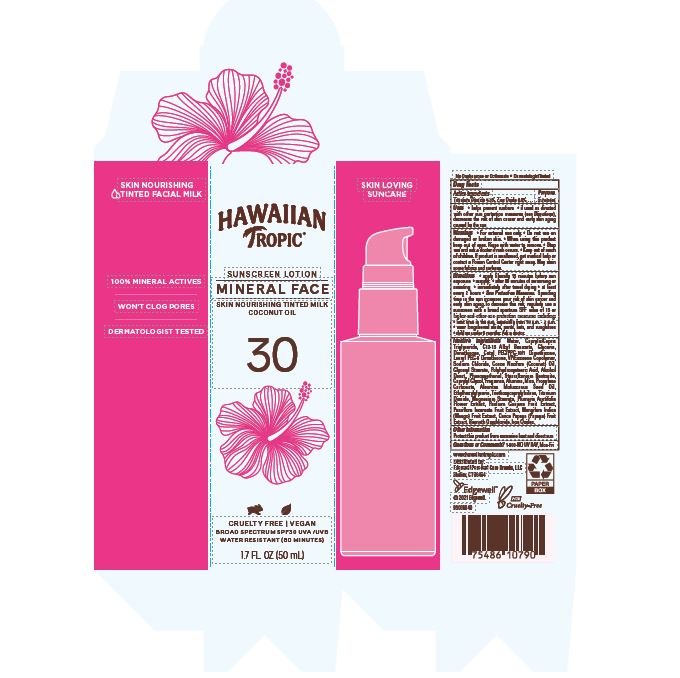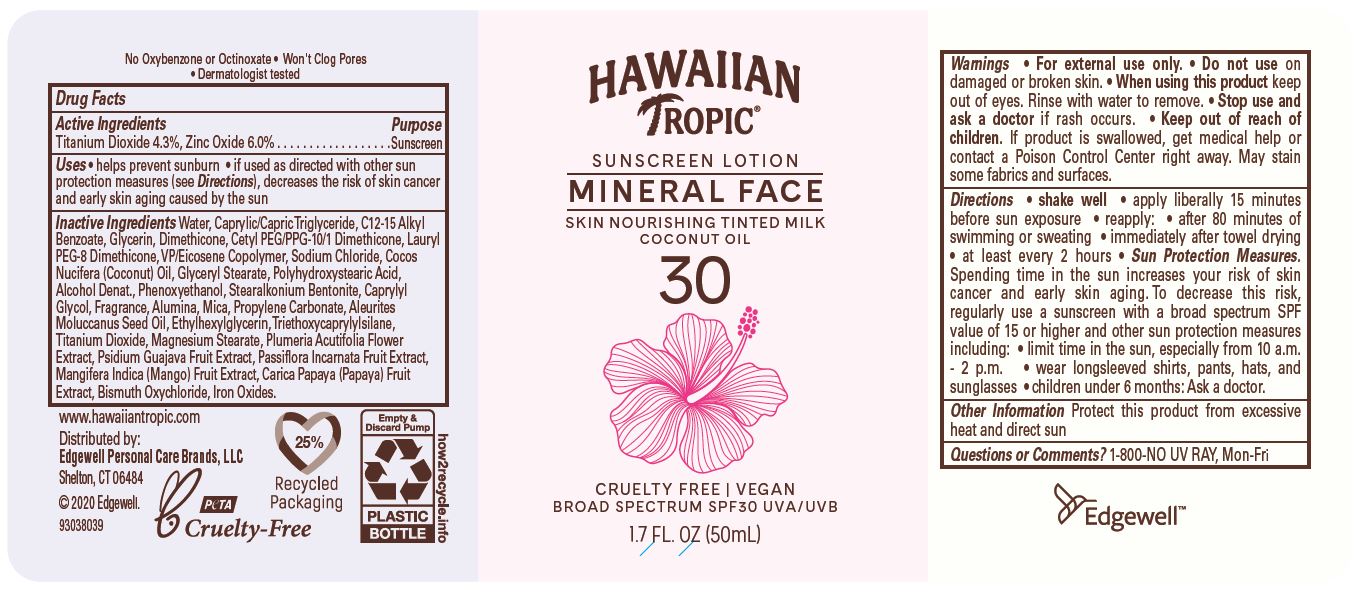 DRUG LABEL: Hawaiian Tropic Mineral Face Skin Nourishing Tinted Milk Coconut Oil SPF30
NDC: 63354-643 | Form: OIL
Manufacturer: Edgewell Personal Care Brands LLC
Category: otc | Type: HUMAN OTC DRUG LABEL
Date: 20251106

ACTIVE INGREDIENTS: ZINC OXIDE 6 g/100 g; TITANIUM DIOXIDE 4.3 g/100 g
INACTIVE INGREDIENTS: GLYCERIN; COCONUT OIL; GLYCERYL MONOSTEARATE; CAPRYLYL GLYCOL; GUAVA; PLUMERIA RUBRA FLOWER; PASSIFLORA INCARNATA FRUIT; MANGO; SODIUM CHLORIDE; MICA; ALKYL (C12-15) BENZOATE; ALCOHOL; KUKUI NUT OIL; PAPAYA; ETHYLHEXYLGLYCERIN; CETYL PEG/PPG-10/1 DIMETHICONE (HLB 2); PHENOXYETHANOL; WATER; MEDIUM-CHAIN TRIGLYCERIDES; DIMETHICONE; BISMUTH OXYCHLORIDE; TRIETHOXYCAPRYLYLSILANE; POLYHYDROXYSTEARIC ACID (2300 MW); ALUMINUM OXIDE; PROPYLENE CARBONATE

Active Ingredients

Titanium Dioxide 4.3%, Zinc Oxide 6.0% .

Purpose

Sunscreen

Uses

• helps prevent sunburn • if used as directed
with other sun protection measures (see Directions),
decreases the risk of skin cancer and early skin aging
caused by the sun

Warnings

For external use only.

May stain some fabrics and surfaces.

Do not use

on damaged or broken skin.

When using this product

keep out of eyes. Rinse with water to remove.

Stop use and ask a doctor

if rash occurs.

Keep out of reach of children.

If product is swallowed, get medical help or contact a Poison Control Center right away.

Directions

• apply liberally 15 minutes before sun
exposure • reapply: • after 80 minutes of swimming or
sweating • immediately after towel drying • at least
every 2 hours • Sun Protection Measures. Spending
time in the sun increases your risk of skin cancer and
early skin aging. To decrease this risk, regularly use a
sunscreen with a broad spectrum SPF value of 15 or
higher and other sun protection measures including:
• limit time in the sun, especially from 10 a.m. - 2 p.m.
• wear longsleeved shirts, pants, hats, and sunglasses
• children under 6 months: Ask a doctor.

Inactive Ingredients

Water, Caprylic/Capric Triglyceride, C12‐15 Alkyl Benzoate, Glycerin, Dimethicone, Cetyl PEG/PPG‐10/1 Dimethicone, Lauryl PEG‐8 Dimethicone, VP/Eicosene Copolymer, Sodium Chloride, Cocos Nucifera (Coconut) Oil, Glyceryl Stearate, Polyhydroxystearic Acid, Alcohol Denat., Phenoxyethanol, Stearalkonium Bentonite, Caprylyl Glycol, Fragrance, Alumina, Mica, Propylene Carbonate, Aleurites Moluccanus Seed Oil, Ethylhexylglycerin, Triethoxycaprylylsilane, Titanium Dioxide, Magnesium Stearate, Plumeria Acutifolia Flower Extract, Psidium Guajava Fruit Extract, Passiflora Incarnata Fruit Extract, Mangifera Indica (Mango) Fruit Extract, Carica Papaya (Papaya) Fruit Extract, Bismuth Oxychloride, Iron Oxides.

Other Information

Protect this product from excessive heat and direct sun

Questions or Comments?

1-800-NO UV RAY, Mon-Fri

PRINCIPAL DISPLAY PANEL

HAWAIIAN

TROPIC

SUNSCREEN LOTION

MINERAL FACE

SKIN NOURISHING TINTED MILK

COCONUT OIL

30

CRUELTY FREE | VEGAN
BROAD SPECTRUM SPF30 UVA/UVB
WATER RESISTANT (80 MINUTES)

1.7 FL. OZ (50 mL)